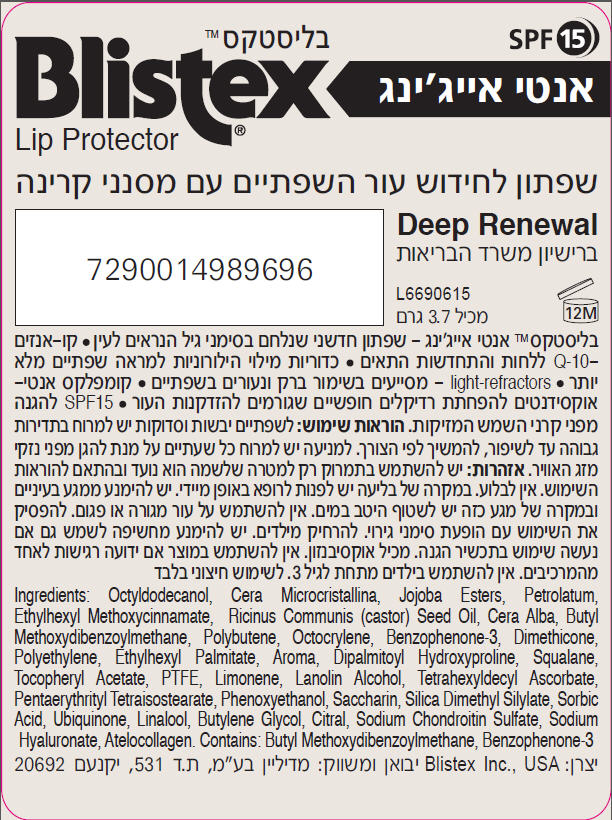 DRUG LABEL: Blistex Deep Renewal International
NDC: 10157-9836 | Form: STICK
Manufacturer: Blistex Inc.
Category: otc | Type: HUMAN OTC DRUG LABEL
Date: 20160429

ACTIVE INGREDIENTS: DIMETHICONE 2 g/100 g; OCTINOXATE 7.5 g/100 g; OXYBENZONE 2.5 g/100 g
INACTIVE INGREDIENTS: OCTYLDODECANOL; Hydrogenated jojoba oil, randomized; MICROCRYSTALLINE WAX; PETROLATUM; CASTOR OIL; YELLOW WAX; POLYBUTENE (1400 MW); HIGH DENSITY POLYETHYLENE; POLYTETRAFLUOROETHYLENE; ETHYLHEXYL PALMITATE; SILICA DIMETHYL SILYLATE; BUTYLENE GLYCOL; HYALURONATE SODIUM; SQUALANE; DIPALMITOYL HYDROXYPROLINE; .ALPHA.-TOCOPHEROL ACETATE; LANOLIN ALCOHOLS; PENTAERYTHRITYL TETRAISOSTEARATE; CHONDROITIN SULFATE SODIUM (SHARK); MARINE COLLAGEN, SOLUBLE; TETRAHEXYLDECYL ASCORBATE; PHENOXYETHANOL; SACCHARIN; SORBIC ACID; UBIDECARENONE

Blistex® Deep Renewal International

PRINCIPAL DISPLAY PANEL - 3.69 g Cylinder Label

Blistex®
Lip Protector